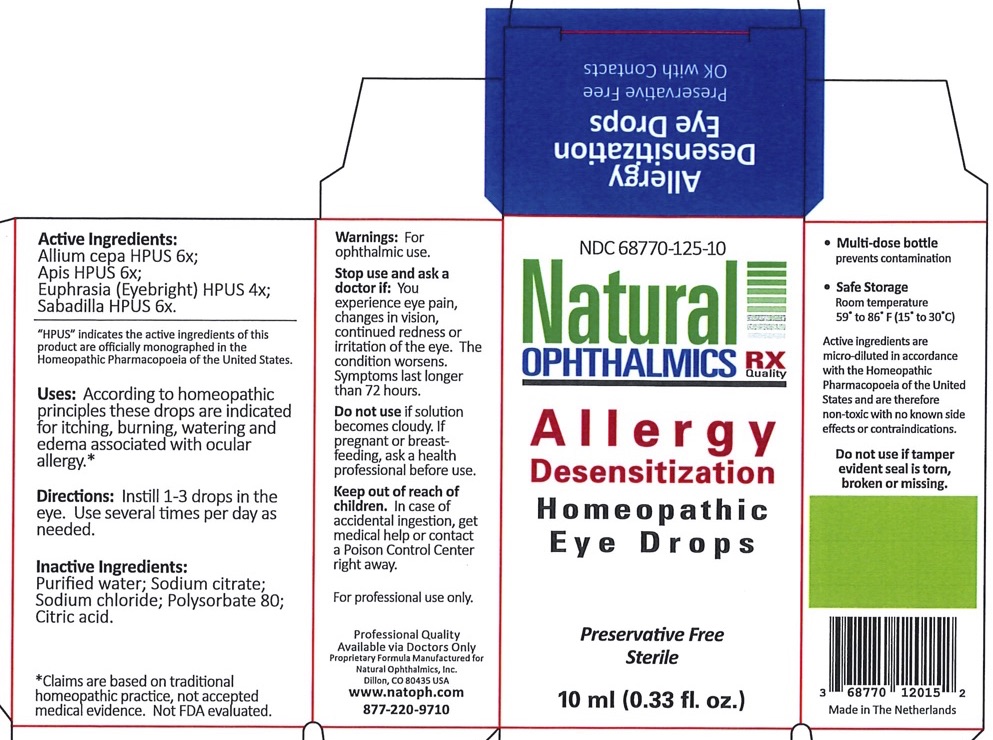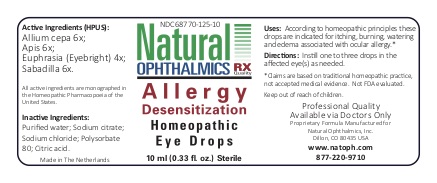 DRUG LABEL: Allergy Desensitization
NDC: 80961-125 | Form: LIQUID
Manufacturer: Peak Manufacturing and Fulfillment Inc
Category: homeopathic | Type: HUMAN OTC DRUG LABEL
Date: 20220113

ACTIVE INGREDIENTS: ONION 6 [hp_X]/1 mL; APIS MELLIFERA 6 [hp_X]/1 mL; SCHOENOCAULON OFFICINALE SEED 6 [hp_X]/1 mL; EUPHRASIA STRICTA 4 [hp_X]/1 mL
INACTIVE INGREDIENTS: WATER; POLYSORBATE 80; CITRIC ACID MONOHYDRATE; SODIUM CHLORIDE

Allergy Desensitization

Homeopathic Purpose

Allium cepa | 6x | Relieves itching, burning
Apis | 6x | Relieves inflammation with burning and stinging
Sabadilla | 6x | Relieve hay fever type symptoms
Euphrasia (Eye-bright) | 4x | General dryness, redness and irritation of the eye and lids

Active Ingredients

Allium cepa | 6x
Apis | 6x
Sabadilla | 6x
Euphrasia (Eye-bright) | 4x

Inactive Ingredients

Sterile water (non-preserved)

Polysorbate 80

Citrates

Sodium chloride

Uses

According to homeopathic principles these drops are indicated for itching, burning, watering and edema associated with ocular allergy.*

Directions

Instill 1-3 drops in the eye. Use several times per day as needed.

Warnings

- For ophthalmic use.
- For Professional Use Only

Keep out of reach of children.

Do not use if solution becomes cloudy. If pregnant or breastfeeding, ask a health professional before use.

Stop use and ask a doctor if: You experience eye pain, changes in vision, continued redness or irritation of the eye. The condition worsens. Symptoms last longer than 72 hours.

Storage

Safe Storage

Room temperature 59o to 86o F (15o to 30o C)

QUESTIONS

Natural Ophthalmlcs, Inc.

Dillon, CO 80435 USA

www.natoph.com

877-220-9710